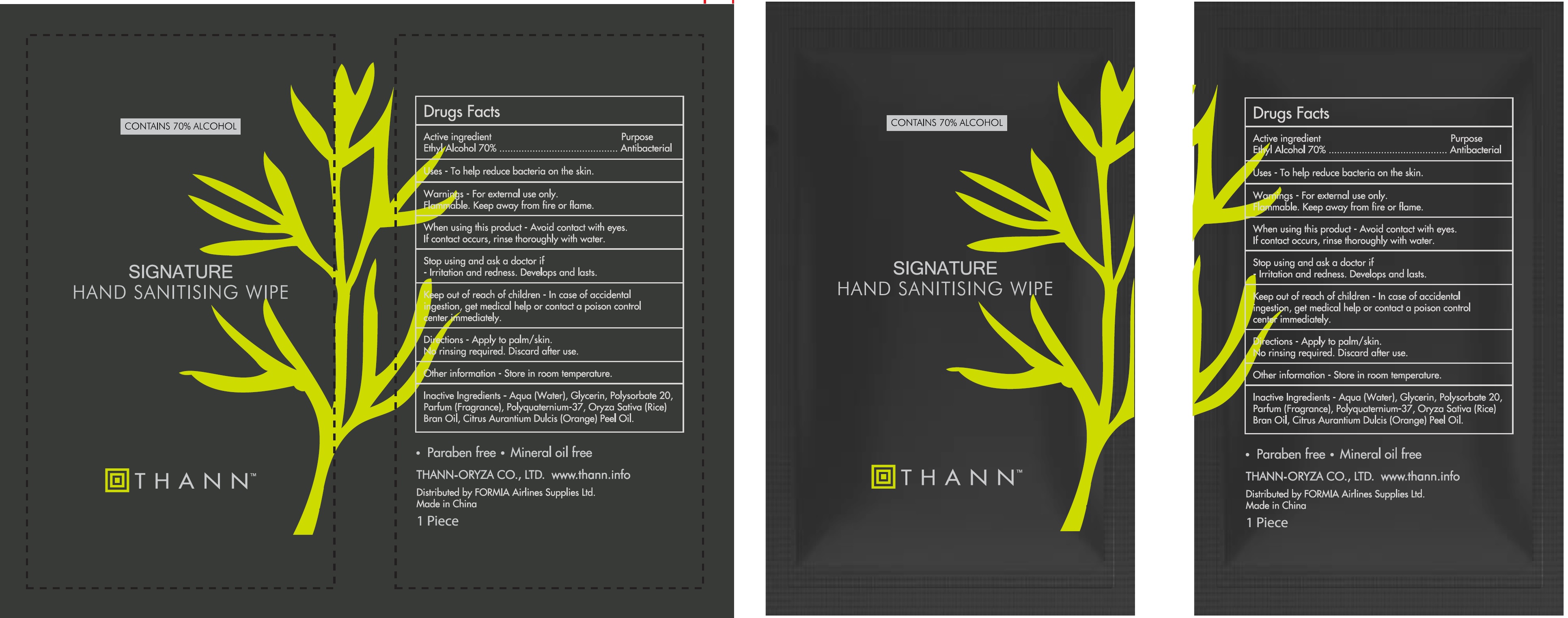 DRUG LABEL: Thann Signature Hand Sanitising Wipe
NDC: 79940-003 | Form: CLOTH
Manufacturer: FORMIA Airline Supplies Ltd
Category: otc | Type: HUMAN OTC DRUG LABEL
Date: 20201029

ACTIVE INGREDIENTS: ALCOHOL 0.7 mL/1 mL
INACTIVE INGREDIENTS: WATER; GLYCERIN; POLYSORBATE 20; POLYQUATERNIUM 37 (200 MPA.S); RICE BRAN OIL; ORANGE OIL

Thann Signature Hand Sanitising Wipe

Active ingredient

Ethyl Alcohol 70%

Purpose

Antibacterial

Uses

- To help reduce bacteria on the skin.

Warnings

-For external use only.
Flammable. Keep away from fire or flame.

When using this product

-Avoid contact with eyes. If contact occurs, rinse thoroughly with water.

Stop using and ask a doctor if

-Irritation and redness. Develops and lasts.

Keep out of reach of children

-In case of accidental ingestion, get medical help or contact a poison control center immediately.

Directions

-Apply to palm/ skin.

No rinsing required. Discard after use.

Other information

-Store in room temperature.

Inactive Ingredients

-Aqua (Water), Glycerin, Polysorbate 20, Parfum (Fragrance), Polyquaternium-37, Oryza Sativa (Rice) Bran Oil, Citrus Aurantium Dulcis (Orange) Peel Oil.